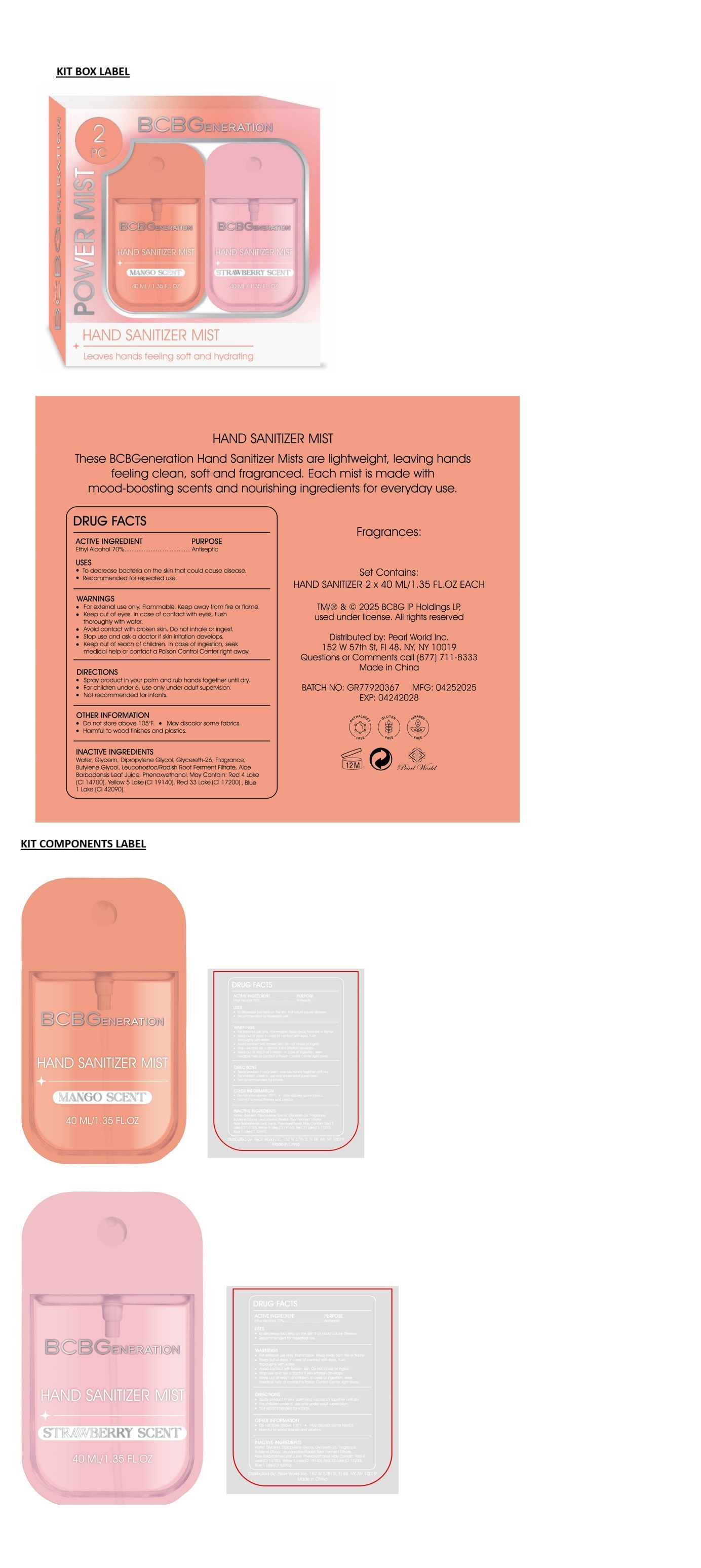 DRUG LABEL: BCBGENERATION HAND SANITIZER MIST SET-MANGO AND STRAWBERRY SCENT
NDC: 69933-309 | Form: KIT | Route: TOPICAL
Manufacturer: Pearl World Inc.
Category: otc | Type: HUMAN OTC DRUG LABEL
Date: 20250509

ACTIVE INGREDIENTS: ALCOHOL 70 mL/100 mL; ALCOHOL 70 mL/100 mL
INACTIVE INGREDIENTS: WATER; GLYCERIN; DIPROPYLENE GLYCOL; GLYCERETH-26; BUTYLENE GLYCOL; LEUCONOSTOC/RADISH ROOT FERMENT FILTRATE; ALOE VERA LEAF JUICE; PHENOXYETHANOL; WATER; GLYCERIN; DIPROPYLENE GLYCOL; GLYCERETH-26; BUTYLENE GLYCOL; LEUCONOSTOC/RADISH ROOT FERMENT FILTRATE; ALOE VERA LEAF JUICE; PHENOXYETHANOL

BCBGENERATION HAND SANITIZER MIST SET-MANGO & STRAWBERRY SCENT

ACTIVE INGREDIENT

Ethyl Alcohol 70%

PURPOSE

Antiseptic

USES

• To decrease bacteria on the skin that could cause disease.
• Recommended for repeated use.

WARNINGS

• For external use only. Flammable. Keep away from fire or flame.
• Keep out of eyes. In case of contact with eyes, flush thoroughly with water.
• Avoid contact with broken skin. Do not inhale or ingest.
• Stop use and ask a doctor if skin irritation develops.

• Keep out of reach of children. In case of ingestion, seek medical help or contact a Poison Control Center right away.

DIRECTIONS

• Spray product in your palm and rub hands together until dry.
• For children under 6, use only under adult supervision.
• Not recommended for infants.

OTHER INFORMATION

• Do not store above 105oF. • May discolor some fabrics.
• Harmful to wood finishes and plastics.

INACTIVE INGREDIENTS

Water, Glycerin, Dipropylene Glycol, Glycereth-26, Fragrance, Butylene Glycol, Leuconostoc/Radish Root Ferment Filtrate, Aloe Barbadensis Leaf Juice, Phenoxyethanol. May Contain: Red 4 Lake (CI 14700), Yellow 5 Lake (CI 19140), Red 33 Lake (CI 17200), Blue 1 Lake (CI 42090).

POWER MIST

Leaves hands feeling soft and hydrating

These BCBGeneration Hand Sanitizer Mists are lightweight, leaving hands feeling clean, soft and fragranced. Each mist is made with mood-boosting scents and nourishing ingredients for everyday use.

TM/® & © 2025 BCBG IP Holdings LP, used under license. All rights reserved

Distributed by: Pearl World Inc.
152 W 57th St. FI 48. NY, NY 10019
Questions or Comments call (877) 711-8333
Made in China

PHTHALATES FREE
GLUTEN FREE
PARABEN FREE